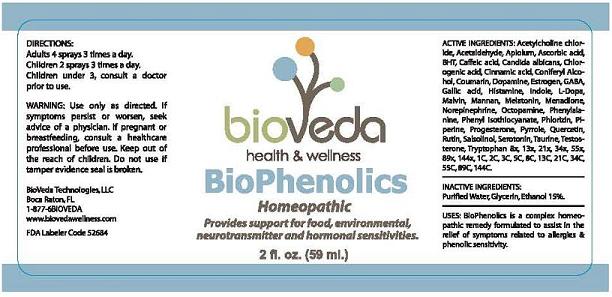 DRUG LABEL: BioPhenolics
NDC: 52684-0025 | Form: SPRAY
Manufacturer: BioVeda
Category: homeopathic | Type: HUMAN OTC DRUG LABEL
Date: 20120517

ACTIVE INGREDIENTS: Acetylcholine chloride 144 [hp_X]/59 mL; Acetaldehyde 144 [hp_X]/59 mL; APIOLE (PARSLEY) 144 [hp_X]/59 mL; Ascorbic acid 144 [hp_X]/59 mL; BUTYLATED HYDROXYTOLUENE 144 [hp_X]/59 mL; Caffeic acid 144 [hp_X]/59 mL; Candida albicans 144 [hp_X]/59 mL; QUINIC ACID 144 [hp_X]/59 mL; Cinnamic acid 144 [hp_X]/59 mL; Coniferyl Alcohol 144 [hp_X]/59 mL; Coumarin 144 [hp_X]/59 mL; Dopamine 144 [hp_X]/59 mL; ESTRONE 144 [hp_X]/59 mL; .GAMMA.-AMINOBUTYRIC ACID 144 [hp_X]/59 mL; Gallic acid 144 [hp_X]/59 mL; Histamine 144 [hp_X]/59 mL; Indole 144 [hp_X]/59 mL; LEVODOPA 144 [hp_X]/59 mL; Malvin 144 [hp_X]/59 mL; YEAST MANNAN 144 [hp_X]/59 mL; MELATONIN 144 [hp_X]/59 mL; Menadione 144 [hp_X]/59 mL; Norepinephrine 144 [hp_X]/59 mL; Octopamine 144 [hp_X]/59 mL; Phenylalanine 144 [hp_X]/59 mL; PHENYL ISOTHIOCYANATE 144 [hp_X]/59 mL; PHLORIZIN 144 [hp_X]/59 mL; Piperine 144 [hp_X]/59 mL; Progesterone 144 [hp_X]/59 mL; PYRROLE 144 [hp_X]/59 mL; Quercetin 144 [hp_X]/59 mL; Rutin 144 [hp_X]/59 mL; Salsolinol 144 [hp_X]/59 mL; Serotonin 144 [hp_X]/59 mL; Taurine 144 [hp_X]/59 mL; Testosterone 144 [hp_X]/59 mL; Tryptophan 144 [hp_X]/59 mL
INACTIVE INGREDIENTS: Water; ALCOHOL; GLYCERIN

BioPhenolics

ACTIVE INGREDIENTS:

Acetylcholine chloride, Acetaldehyde, Apiolum, Ascorbic acid, BHT, Caffeic acid, Candida albicans, Chlorogenic acid, Cinnamic acid, Coniferyl Alcohol, Coumarin, Dopamine, Estrogen, GABA, Gallic acid, Histamine, Indole, L-Dopa, Malvin, Mannan, Melatonin, Menadione, Norepinephrine, Octopamine, Phenylalanine, Phenyli-sothiocyanate, Phlorizin, Piperine, Progesterone, Pyrrole, Quercetin, Rutin, Salsolinol, Serotonin, Taurine, Testosterone, Tryptophan 8X, 13X, 21X, 34X, 55X, 89X, 144X, 1c, 2c, 3c, 5c, 8c, 13c, 21c, 34c, 55c, 89c, 144c

USES:

BioPhenolics is a complex homeopathic remedy formulated to assist in the relief of symptoms related to allergies and phenolic sensitivity.

WARNING:

Use only as directed.

ASK DOCTOR

If symptoms persist or worsen, seek advice of a physician.

PREGNANCY OR BREAST FEEDING

If pregnant or breastfeeding, consult a healthcare professional before use.

Keep out of the reach of children.

Do not use if tamper evidence seal is broken.

DIRECTIONS:

Adults 4 sprays 3 times a day.

Children 2 sprays 3 times a day.

Children under 3, consult a doctor prior to use.

INACTIVE INGREDIENTS:

Purified Water, Glycerin, Ethanol 15%

QUESTIONS:

BioVeda Technologies, LLC

Boca Raton, FL

1-877-6BIOVEDA

www.biovedawellness.com

PRINCIPAL DISPLAY PANEL

BioPhenolics

Homeopathic

Provides support for food, environmental, neurotransmitter and hormonal sensitivities.